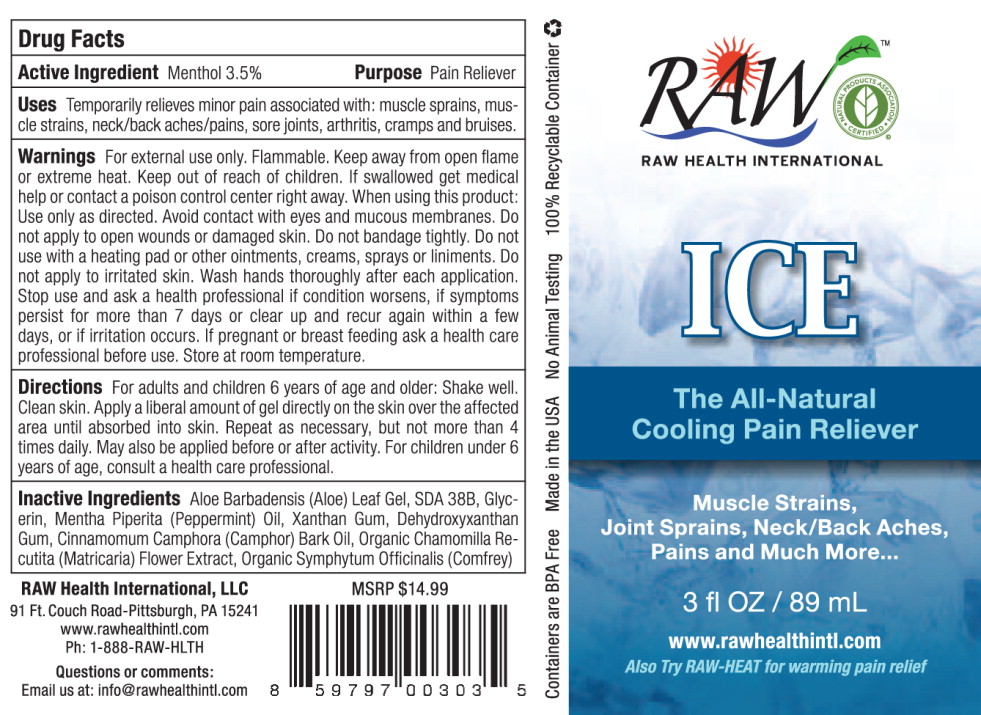 DRUG LABEL: Raw Ice
NDC: 55413-2500 | Form: LIQUID
Manufacturer: Raw Health International, LLC
Category: otc | Type: HUMAN OTC DRUG LABEL
Date: 20130130

ACTIVE INGREDIENTS: menthol 34.79 g/1 L
INACTIVE INGREDIENTS: aloe vera leaf; glycerin; peppermint oil; xanthan gum; camphor oil; matricaria recutita; symphytum uplandicum leaf

Drug Facts

Active Ingredient

Menthol 3.5%

Purpose

Pain Reliever

Uses

Temporarily relieves minor pain associated with: muscle sprains, muscle strains, neck/back aches/pains, sore joints, arthritis, cramps and bruises.

Warnings

For external use only. Flammable. Keep away from open flame or extreme heat.

Keep out of reach of children. If swallowed get medical help or contact a poison control center right away.

When using this product: Use only as directed. Avoid contact with eyes and mucous membranes. Do not apply to open wounds or damaged skin. Do not bandage tightly.

Do not use with a heating pad or other ointments, creams, sprays or liniments. Do not apply to irritated skin. Wash hands thoroughly after each application.

Stop use and ask a health professional if condition worsens, if symptoms persist for more than 7 days or clear up and recur again within a few days, or if irritation occurs. If pregnant or breast feeding ask a health care professional before use. Store at room temperature.

Directions

For adults and children 6 years of age and older: Shake well. Clean skin. Apply a liberal amount of gel directly on the skin over the affected area until absorbed into skin. Repeat as necessary, but not more than 4 times daily. May also be applied before or after activity. For children under 6 years of age, consult a health care professional.

Inactive Ingredients

Aloe Barbadensis (Aloe) Leaf Gel, SDA 38B, Glycerin, Mentha Piperita (Peppermint) Oil, Xanthan Gum, Dehydroxyxanthan Gum, Cinnamomum Camphora (Camphor) Bark Oil, Organic Chamomilla Recutita (Matricaria) Flower Extract, Organic Symphytum Officinalis (Comfrey)

RAW Health International, LLC
91 Ft. Couch Road-Pittsburgh, PA 15241
www.rawhealthintl.com
Ph: 1-888-RAW-HLTH

Questions or comments:

Email us at: info@rawhealthintl.com

MSRP $14.99

PRINCIPAL DISPLAY PANEL – 3 oz. bottle

RAW
RAW HEALTH INTERNATIONAL

ICE

The All-Natural
Cooling Pain Reliever

Muscle Strains,
Joint Sprains, Neck/Back Aches,
Pains and Much More…

3 fl OZ / 89 mL

www.rawhealthintl.com
Also Try RAW-HEAT for warming pain relief